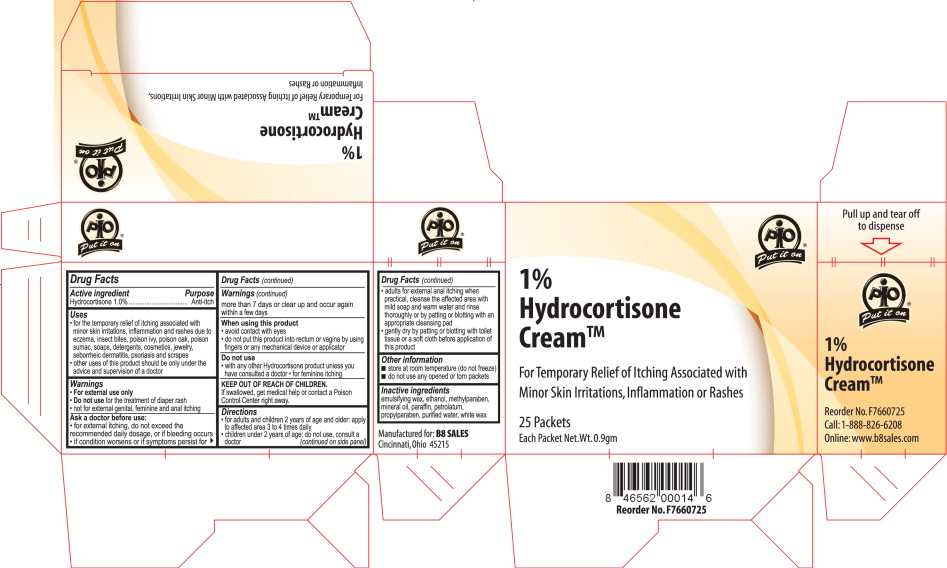 DRUG LABEL: Hydrocortisone
NDC: 50607-5802 | Form: CREAM
Manufacturer: B8 Sales, Inc.
Category: otc | Type: HUMAN OTC DRUG LABEL
Date: 20100402

ACTIVE INGREDIENTS: hydrocortisone 10 mg/1 g
INACTIVE INGREDIENTS: Ethanol; methylparaben; mineral oil; paraffin; petrolatum; propylparaben; water; white wax

PIO Put it on®
1% Hydrocortisone Cream™

For Temporary Relief of Itching Associated with Minor Skin Irritations, Inflammation or Rashes

25 Packets

Each Packet Net.Wt.0.9gm

Active ingredient

Hydrocortisone 1.0%

Purpose

Anti-itch

Uses

- for the temporary relief of itching associated with minor skin irritations, inflammation and rashes due to eczema, insect bites, poison ivy, poison oak, poison sumac, soaps, detergents, cosmetics, jewelry, seborrheic dermatitis, psoriasis and scrapes
- other uses of this product should be only under the advice and supervision of a doctor

Warnings

- For external use only
- Do not use for the treatment of diaper rash
- not for external genital, feminine and anal itching

Ask a doctor before use:

- for external itching, do not exceed the recommended daily dosage, or if bleeding occurs
- if condition worsens or if symptoms persist for more than 7 days or clear up and occur again within a few days

When using this product

- avoid contact with eyes
- do not put this product into rectum or vagina by using fingers or any mechanical device or applicator

Do not use

- with any other Hydrocortisone product unless you have consulted a doctor • for feminine itching

KEEP OUT OF REACH OF CHILDREN.

If swallowed, get medical help or contact a Poison Control Center right away.

Directions

- for adults and children 2 years of age and older apply
  to affected area 3 to 4 times daily
- children under 2 years of age: do not use, consult a doctor
- adults for external anal itching when practical, cleanse the affected area with mild soap and warm water and rinse thoroughly or by patting or blotting with an appropriate cleansing pad
- gently dry by patting or blotting with toilet tissue or a soft cloth before application of this product

Other information

- store at room temperature (do not freeze)
- do not use any opened or torn packets

Inactive ingredients

emulsifying wax, ethanol, methylparaben, mineral oil, paraffin, petrolatum, propylparaben, purified water, white wax

Manufactured for: B8 SALES

Cincinnati,Ohio 45215

Principal Display Panel

1% Hydrocortisone Cream – Carton Label

PIO Put it on®

1% Hydrocortisone Cream™

For Temporary Relief of Itching Associated with Minor Skin Irritations, Inflammation or Rashes

25 Packets

Each Packet Net.Wt.0.9gm